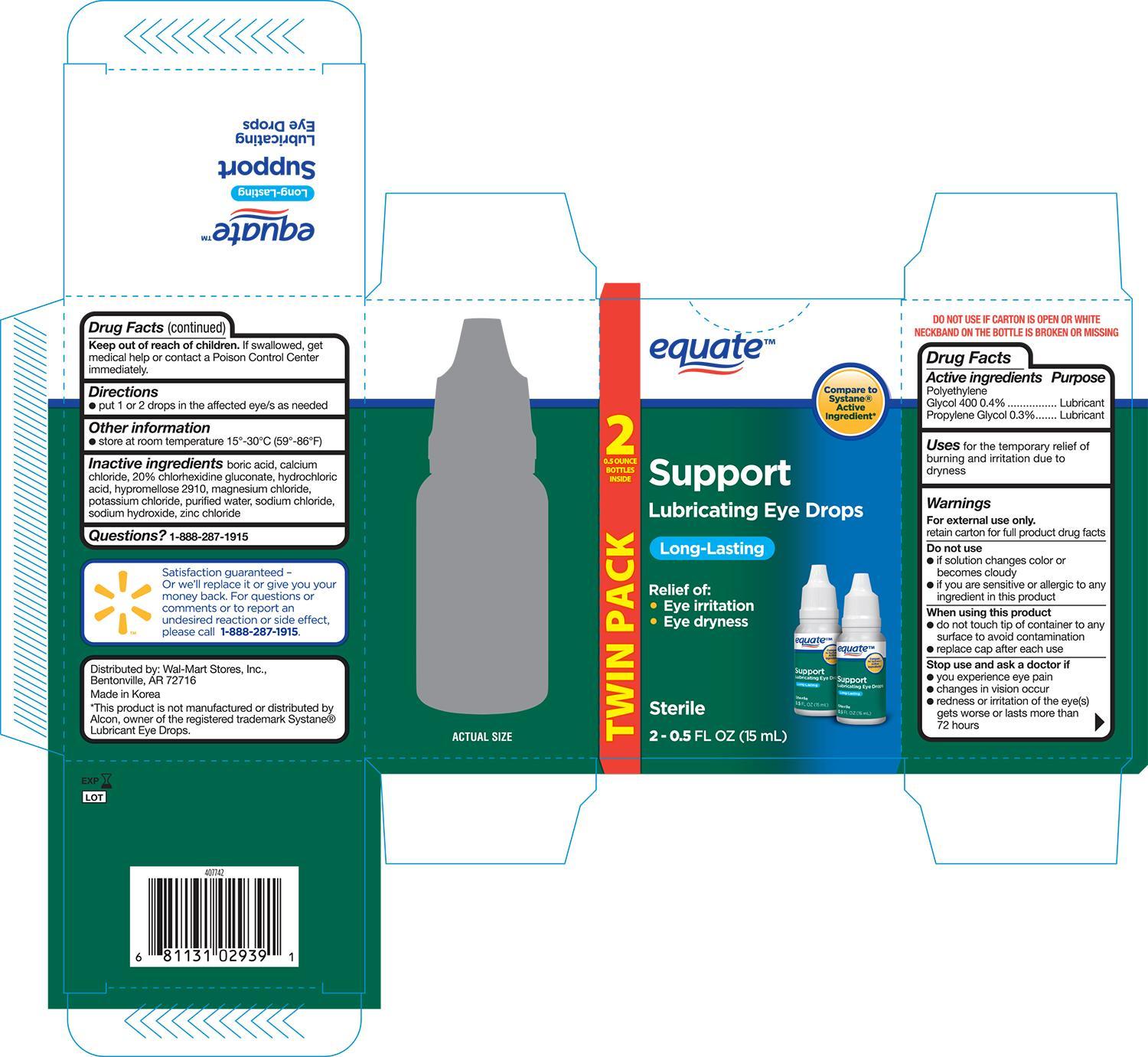 DRUG LABEL: EQUATE LUBRICANT EYE
NDC: 49035-939 | Form: SOLUTION/ DROPS
Manufacturer: WAL-MART STORES INC
Category: otc | Type: HUMAN OTC DRUG LABEL
Date: 20141230

ACTIVE INGREDIENTS: POLYETHYLENE GLYCOL 400 4 mg/1 mL; PROPYLENE GLYCOL 3 mg/1 mL
INACTIVE INGREDIENTS: BORIC ACID; CALCIUM CHLORIDE; CHLORHEXIDINE GLUCONATE; HYDROCHLORIC ACID; HYPROMELLOSE 2910 (5 MPA.S); MAGNESIUM CHLORIDE; POTASSIUM CHLORIDE; WATER; SODIUM CHLORIDE; SODIUM HYDROXIDE; ZINC CHLORIDE

Active ingredients Purpose

Polyethylene Glycol 400 0.4%--------------------------------- Lubricant

Propylene Glycol 0.3%----------------------------------------- Lubricant

Uses

For the temporary relief of burning and irritation due to eye dryness.

Warnings

For external use only.
retain carton for full product drug facts

Do not use

- if solution changes color or becomes cloudy
- if you are sensitive or allergic to any ingredient in this product

When using this product

- do not touch tip of container to any surface to avoid contamination
- replace cap after each use

Stop use and ask a doctor if

- you experience eye pain
- changes in vision occur
- redness or irritation of the eye(s) gets worse or lasts more than 72 hours

Keep out of reach of children

If swallowed, get medical help or contact a Poison Control Center immediately

Directions

- Put 1 or 2 drops in the affected eye/s as needed

Other information

- store at room temperature 15o-30oC (59o-86oF)

Inactive ingredients

boric acid, calcium chloride, 20% chlorhexidine gluconate, hydrochloric acid, hypromellose 2910, magnesium chloride, potassium chloride, purified water, sodium chloride, sodium hydroxide, zinc chloride

DOSAGE AND ADMINISTRATION

DISTRIBUTED BY:

WAL-MART STORES, INC.

BENTONVILLE, AR 72716

MADE IN KOREA